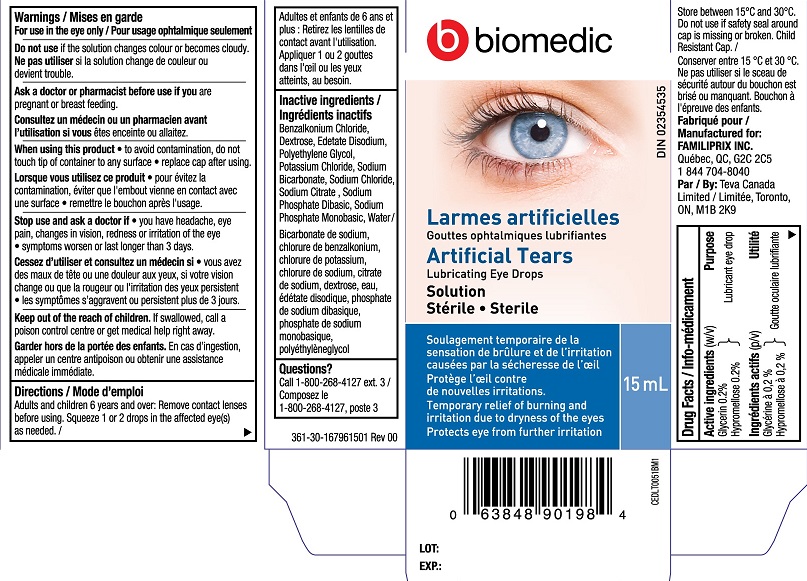 DRUG LABEL: Biomedic Artificial Tears
NDC: 55651-031 | Form: LIQUID
Manufacturer: KC Pharmaceuticals, Inc.
Category: otc | Type: HUMAN OTC DRUG LABEL
Date: 20251231

ACTIVE INGREDIENTS: GLYCERIN 0.2 g/100 mL; HYPROMELLOSE, UNSPECIFIED 0.2 g/100 mL
INACTIVE INGREDIENTS: POLYETHYLENE GLYCOL, UNSPECIFIED; BENZALKONIUM CHLORIDE; DEXTROSE; EDETATE DISODIUM; POTASSIUM CHLORIDE; WATER; SODIUM BICARBONATE; SODIUM CHLORIDE; SODIUM CITRATE; SODIUM PHOSPHATE, DIBASIC; SODIUM PHOSPHATE, MONOBASIC

Biomedic Artificial Tears 15mL (MFR - EXPORT)